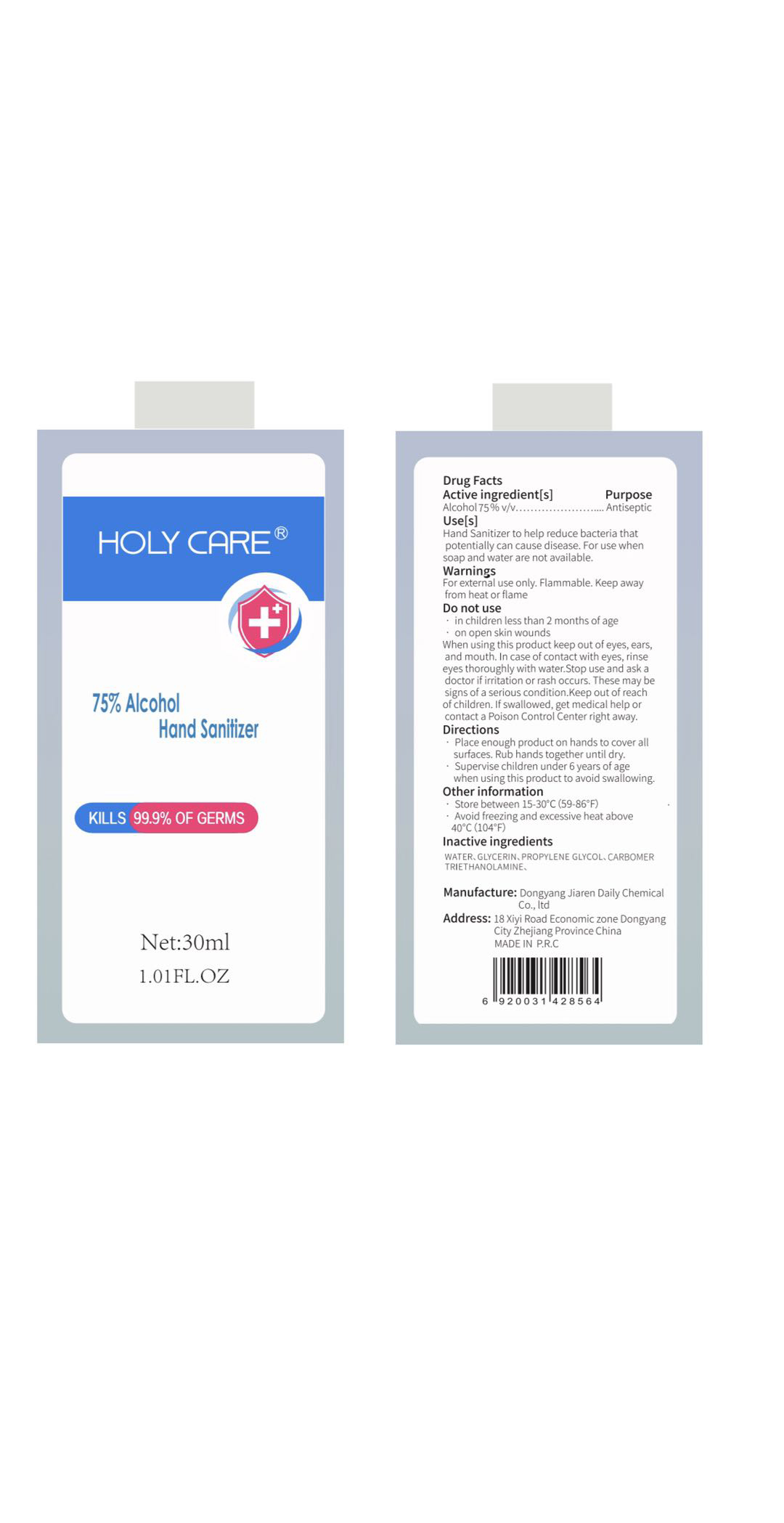 DRUG LABEL: Holy Care 75 Percent Alcohol Hand Sanitizer
NDC: 77148-001 | Form: SOLUTION
Manufacturer: DONGYANG CITY JIAREN DAILY COSMETIC CO., LTD.
Category: otc | Type: HUMAN OTC DRUG LABEL
Date: 20200504

ACTIVE INGREDIENTS: ALCOHOL 75 mL/100 mL
INACTIVE INGREDIENTS: GLYCERIN; PROPYLENE GLYCOL; WATER; CARBOMER 934; TROLAMINE

NA

Active Ingredient(s)

Alcohol 75% v/v

Purpose

Antiseptic

Use

Hand sanitizer to help decrease bacteria that potentially can cause disease

For use when soap and water is not available

Warnings

For external use only. Flammable. Keep away from heat or flame

Do not use

- in children less than 2 months of age
- on open skin wounds

When using this product keep out of eyes, ears, and mouth. In case of contact with eyes, rinse eyes thoroughly with water.

Stop use and ask a doctor if irritation or rash occurs. These may be signs of serious condition

Keep out of reach of children. If swallowed, get medical help or contact a Poison Control Center right away.

Directions

- Place enough product on the skin to cover all surface
- Rub hands together untill dry
- Supervise children under 6 years of age whenusing this product to avoid swallowing

Other information

- Store between 15-30C (59-86F)
- Avoid freezing and excessive heat above 40C (104F)

Inactive ingredients

Water, propylene glycol, glycerin, carbomer, triethanolamine